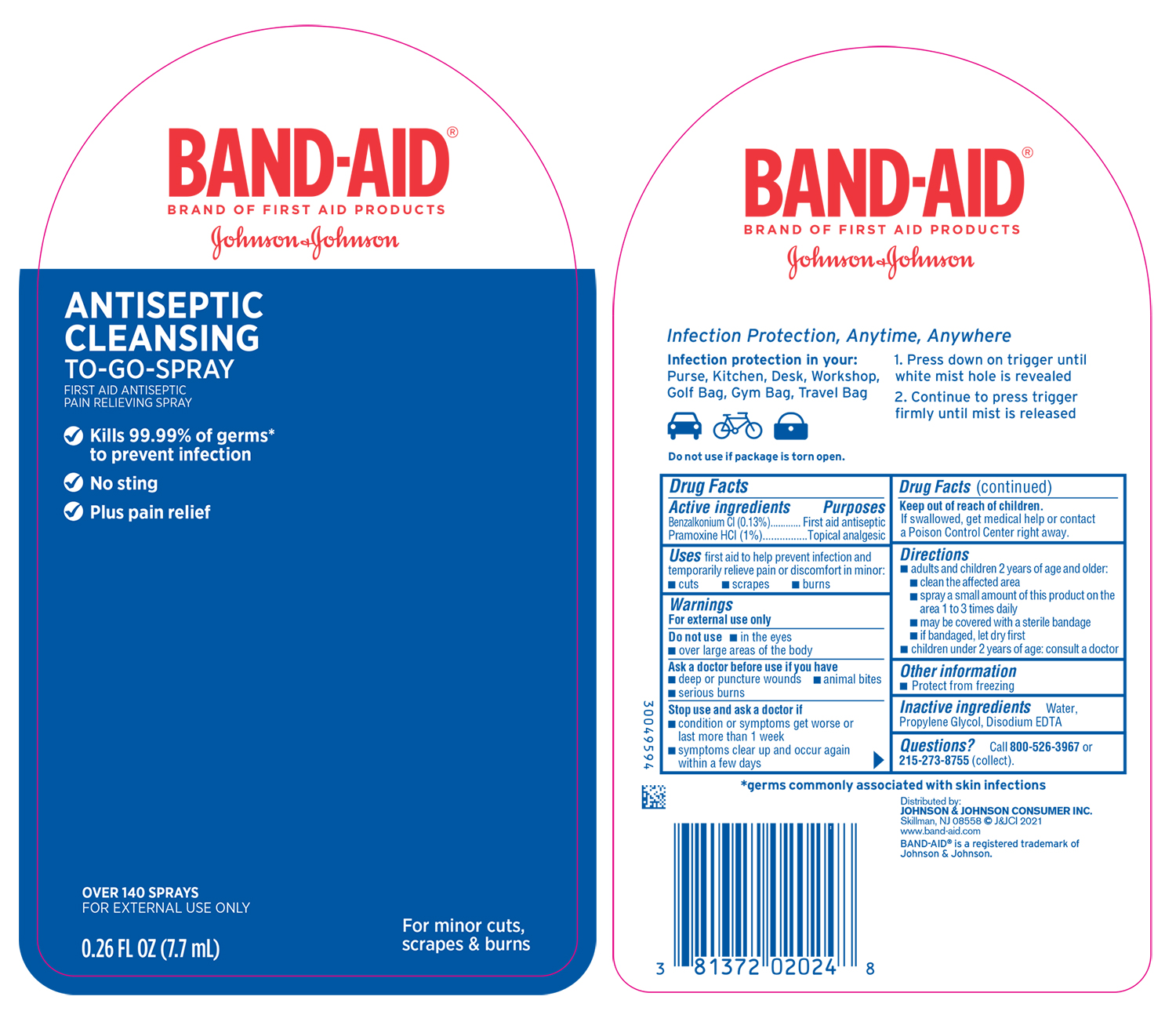 DRUG LABEL: Band Aid Antiseptic Cleansing To Go
NDC: 69968-0727 | Form: SPRAY
Manufacturer: Kenvue Brands LLC
Category: otc | Type: HUMAN OTC DRUG LABEL
Date: 20241106

ACTIVE INGREDIENTS: PRAMOXINE HYDROCHLORIDE 10 mg/1 mL; BENZALKONIUM CHLORIDE 1.3 mg/1 mL
INACTIVE INGREDIENTS: WATER; PROPYLENE GLYCOL; EDETATE DISODIUM

Band Aid Antiseptic Cleansing To Go

Drug Facts

Active ingredient

Benzalkonium Cl (0.13%)

Pramoxine HCl (1%)

Purposes

First aid antiseptic

Topical analgesic

Use

first aid to help prevent infection and temporarily relieve pain or discomfort in minor: · cuts · scrapes · burns

Warnings

- For external use only.

Do not use · in the eyes · over large area of the body

- Ask a doctor before use if you have · deep or puncture wounds · animal bites · serious burns

- Stop use and ask a doctor if · condition or symptoms get worse or last more than 1 week · symptoms clear up and occur again within a few days

Keep out of reach of children.

If swallowed, get medical help or contact a Poison Control Center right away.

Directions

adults and children 2 years of age and older:

clean the affected area
spray a small amount of this product on the area 1 to 3 times daily
may be covered with a sterile bandage
if bandaged, let dry first

children under 2 years of age: consult a doctor

Other information

Protect from freezing

Inactive ingredients

Water, Propylene Glycol, Disodium EDTA

Questions?

call 800-526-3967 or 215-273-8755 (collect).

Distributed by:
JOHNSON & JOHNSON CONSUMER INC.
Skillman, NJ 08558

PRINCIPAL DISPLAY PANEL - 7.7mL Vial Blister pack

BAND-AID®

BRAND OF FIRST AID PRODUCTS

Johnson & Johnson

ANTISEPTIC

CLEANSING

TO-GO-SPRAY

FIRST AID ANTIBIOTIC

PAIN RELEIVING SPRAY

Kills 99.99% of germs*

to prevent infection

No sting

Plus pain relief

OVER 140 SPRAYS

FOR EXTERNAL USE ONLY

0.26 FL OZ (7.7mL)

For minor cuts,

scrapes & burns